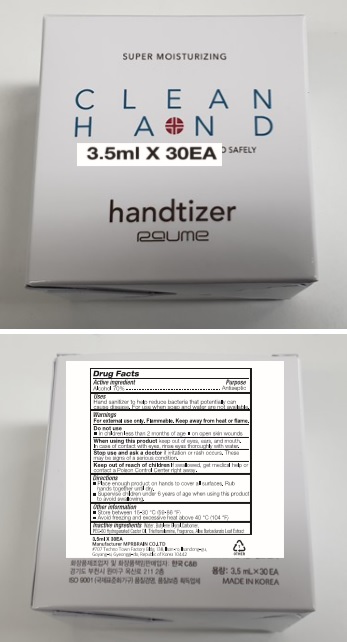 DRUG LABEL: CLEAN HAND RAUME
NDC: 74741-3530 | Form: GEL
Manufacturer: MPRBRAIN CO.LTD
Category: otc | Type: HUMAN OTC DRUG LABEL
Date: 20200505

ACTIVE INGREDIENTS: ALCOHOL 2.45 mL/3.5 mL
INACTIVE INGREDIENTS: CARBOMER HOMOPOLYMER, UNSPECIFIED TYPE; PEG-60 HYDROGENATED CASTOR OIL; BUTYLENE GLYCOL; WATER; TROLAMINE; ALOE VERA LEAF

CLEAN HAND RAUME 3.5 ml X 30 : 74741-3530-2